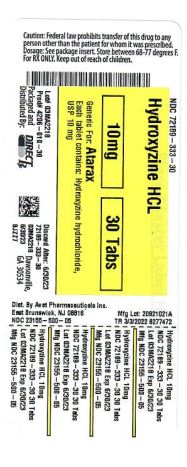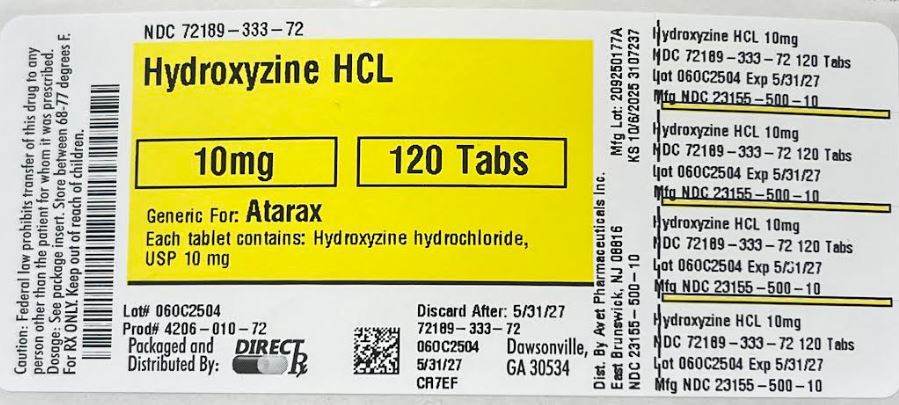 DRUG LABEL: HYDROXYZINE HYDROCHLORIDE
NDC: 72189-333 | Form: TABLET
Manufacturer: Direct Rx
Category: prescription | Type: HUMAN PRESCRIPTION DRUG LABEL
Date: 20251006

ACTIVE INGREDIENTS: HYDROXYZINE DIHYDROCHLORIDE 10 mg/1 1
INACTIVE INGREDIENTS: SILICON DIOXIDE; HYPROMELLOSES; MAGNESIUM STEARATE; CROSPOVIDONE; TITANIUM DIOXIDE; ANHYDROUS LACTOSE; CELLULOSE, MICROCRYSTALLINE; POLYSORBATE 80; POLYETHYLENE GLYCOL, UNSPECIFIED

Hydroxyzine HCL

HOW SUPPLIED

Hydroxyzine Hydrochloride Tablets, USP are available as follows:

10 mg tablets: round, film coated white tablets. Debossed H on one side and 500 on the reverse side. They are available as follows:

Bottles of 100: NDC 23155-500-01

Bottles of 500: NDC 23155-500-05

Bottles of 1000: NDC 23155-500-10

25 mg tablets: round, film coated white tablets. Debossed H over 501 on one side and plain on the reverse side. They are available as follows:

Bottles of 100: NDC 23155-501-01

Bottles of 500: NDC 23155-501-05

Bottles of 1000: NDC 23155-501-10

50 mg tablets: round, film coated white tablets. Debossed H over 502 on one side and plain on the reverse side. They are available as follows:

Bottles of 100: NDC 23155-502-01

Bottles of 500: NDC 23155-502-05

Bottles of 1000: NDC 23155-502-10

Dispense in a tight container as defined in the USP, with a child-resistant closure (as required).

Store at 20° to 25°C (68° to 77°F) [See USP Controlled Room Temperature].

KEEP THIS AND ALL MEDICATIONS OUT OF THE REACH OF CHILDREN.

Distributed by:

Avet Pharmaceuticals Inc.

East Brunswick, NJ 08816

1.866.901.DRUG (3784)

logo
51U000000193US07

Rev. 10/2019

DOSAGE AND ADMINISTRATION

For symptomatic relief of anxiety and tension associated with psychoneurosis and as an adjunct in organic disease states in which anxiety is manifested: adults, 50 to 100 mg q.i.d.; children under 6 years, 50 mg daily in divided doses; children over 6 years, 50 to 100 mg daily in divided doses.

For use in the management of pruritus due to allergic conditions such as chronic urticaria and atopic and contact dermatoses and in histamine-mediated pruritus: adults, 25 mg t.i.d. or q.i.d.; children under 6 years, 50 mg daily in divided doses; children over 6 years, 50 to 100 mg daily in divided doses.

As a sedative when used as a premedication and following general anesthesia: 50 to 100 mg for adults and 0.6 mg/kg of body weight in children.

When treatment is initiated by the intramuscular route of administration, subsequent doses may be administered orally.

As with all potent medication, the dosage should be adjusted according to the patient's response to therapy.

OVERDOSAGE

The most common manifestation of hydroxyzine overdosage is hypersedation. Other reported signs and symptoms were convulsions, stupor, nausea and vomiting. As in the management of overdosage with any drug, it should be borne in mind that multiple agents may have been taken.

If vomiting has not occurred spontaneously, it should be induced. Immediate gastric lavage is also recommended. General supportive care, including frequent monitoring of the vital signs and close observation of the patient, is indicated. Hypotension, though unlikely, may be controlled with intravenous fluids and levarterenol or metaraminol. Do not use epinephrine as hydroxyzine counteracts its pressor action.

Hydroxyzine overdose may cause QT prolongation and Torsade de Pointes. ECG monitoring is recommended in cases of hydroxyzine overdose.

There is no specific antidote. It is doubtful that hemodialysis would be of any value in the treatment of overdosage with hydroxyzine. However, if other agents such as barbiturates have been ingested concomitantly, hemodialysis may be indicated. There is no practical method to quantitate hydroxyzine in body fluids or tissue after its ingestion or administration.

INDICATIONS AND USAGE

For symptomatic relief of anxiety and tension associated with psychoneurosis and as an adjunct in organic disease states in which anxiety is manifested.

Useful in the management of pruritus due to allergic conditions such as chronic urticaria and atopic and contact dermatoses and in histamine-mediated pruritus.

As a sedative when used as a premedication and following general anesthesia, hydroxyzine may potentiate meperidine and barbiturates, so their use in pre-anesthetic adjunctive therapy should be modified on an individual basis. Atropine and other belladonna alkaloids are not affected by the drug. Hydroxyzine is not known to interfere with the action of digitalis in any way and it may be used concurrently with this agent.

The effectiveness of hydroxyzine as an antianxiety agent for long term use, that is more than 4 months, has not been assessed by systematic clinical studies. The physician should reassess periodically the usefulness of the drug for the individual patient.

CLINICAL PHARMACOLOGY

Hydroxyzine hydrochloride is unrelated chemically to the phenothiazines, reserpine, meprobamate or the benzodiazepines. Hydroxyzine is not a cortical depressant, but its action may be due to a suppression of activity in certain key regions of the subcortical area of the central nervous system.

Primary skeletal muscle relaxation has been demonstrated experimentally. Bronchodilator activity, and antihistaminic and analgesic effects have been demonstrated experimentally and confirmed clinically. An antiemetic effect, both by the apomorphine test and the veriloid test, has been demonstrated.

Pharmacological and clinical studies indicate that hydroxyzine in therapeutic dosage does not increase gastric secretion or acidity and in most cases has mild antisecretory activity.

Hydroxyzine is rapidly absorbed from the gastrointestinal tract and hydroxyzine's clinical effects are usually noted within 15 to 30 minutes after oral administration.

DESCRIPTION

Hydroxyzine hydrochloride, USP has the chemical name of (±)-2-[2-[4-(p-Chloro-α-phenylbenzyl)-1-piperazinyl]ethoxy]ethanol dihydrochloride.

stucture
Molecular Formula: C21H27ClN2O2 · 2HCl Molecular Weight: 447.83

Hydroxyzine hydrochloride, USP occurs as a white, odorless powder which is very soluble in water.

Each tablet for oral administration contains 10 mg, 25 mg, or 50 mg hydroxyzine hydrochloride, USP. Inactive ingredients include anhydrous lactose, colloidal silicon dioxide, crospovidone, hypromellose, magnesium stearate, microcrystalline cellulose, polyethylene glycol, polysorbate and titanium dioxide.